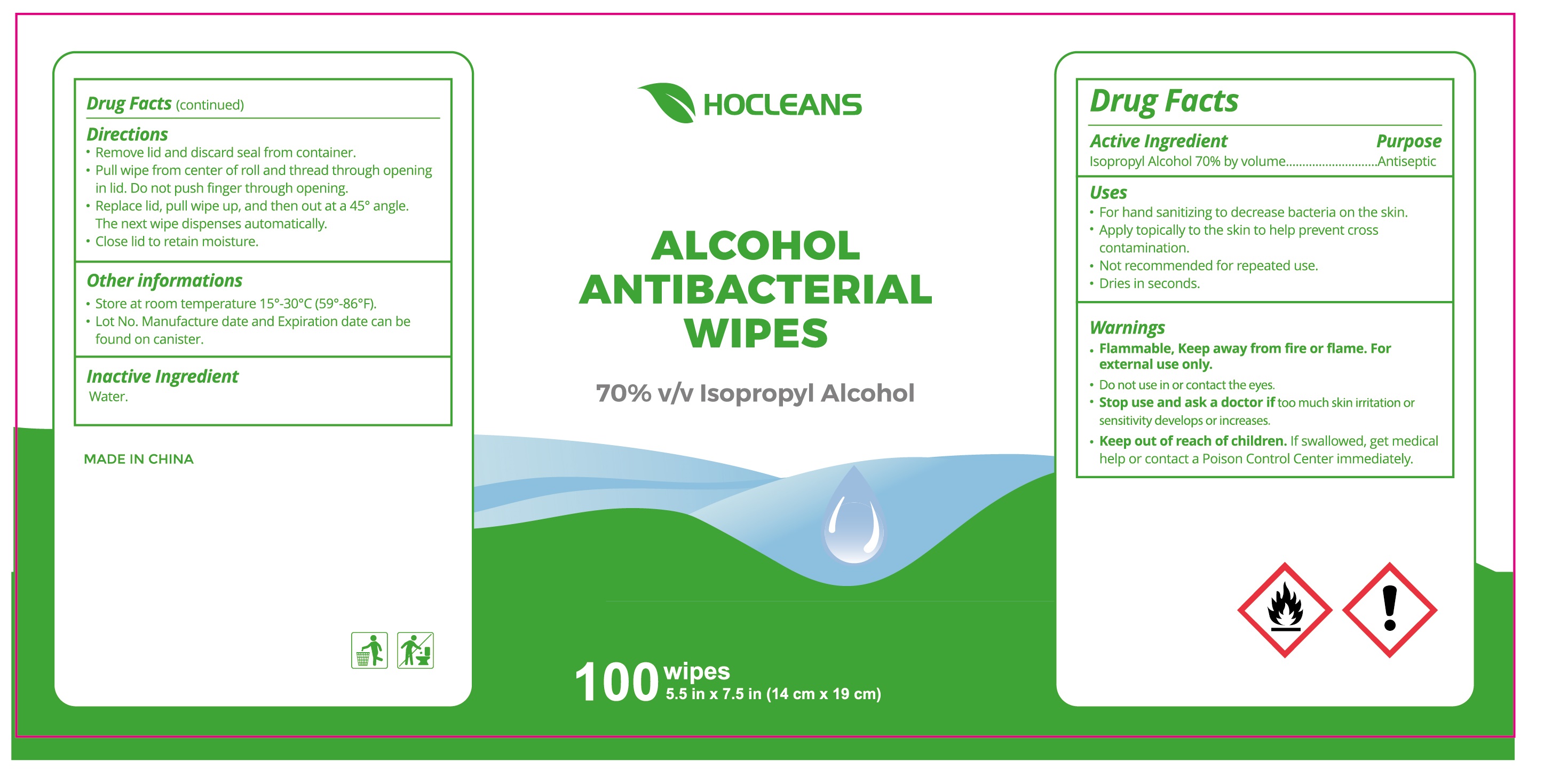 DRUG LABEL: Hocleans IPA Wipe
NDC: 75109-509 | Form: CLOTH
Manufacturer: Kangna (Zhejiang) Medical Supplies Co., Ltd.
Category: otc | Type: HUMAN OTC DRUG LABEL
Date: 20220114

ACTIVE INGREDIENTS: ISOPROPYL ALCOHOL 70 mL/100 mL
INACTIVE INGREDIENTS: WATER

75109-509 Hocleans IPA Wipe 70% Isopropyl Alcohol

Active Ingredient

Isopropyl Alcohol 70% by volume

Purpose

Antiseptic

USE

for hand sanitizing to decrease bacteria on the skin

apply topically to the skin to help prevent cross contamination

not recommended for repeated use

dries in seconds

Warning

●Flammable, Keep away from fire or flame. For
external use only.
●Do not use in or contact the eyes.
●Stop use and ask a doctor if too much skin irritation or
sensitivity develops or increases.

Keep out of reach of children unless under adult supervision.

If swallowed, get medical help or call Poison Control Center immediately.

Directions

●Remove lid and discard seal from container.
●Pull wipe from center of roll and thread through opening
in lid. Do not push finger through opening.
Replace lid, pull wipe up, and then out at a 45° angle.
The next wipe dispenses automatically.
●Close lid to retain moisture.
Other informations
●Store at room temperature 15*-30°C (59*-86°F).
●Lot No. Manufacture date and Expiration date can be
found on canister.

Inactive ingredients

Water